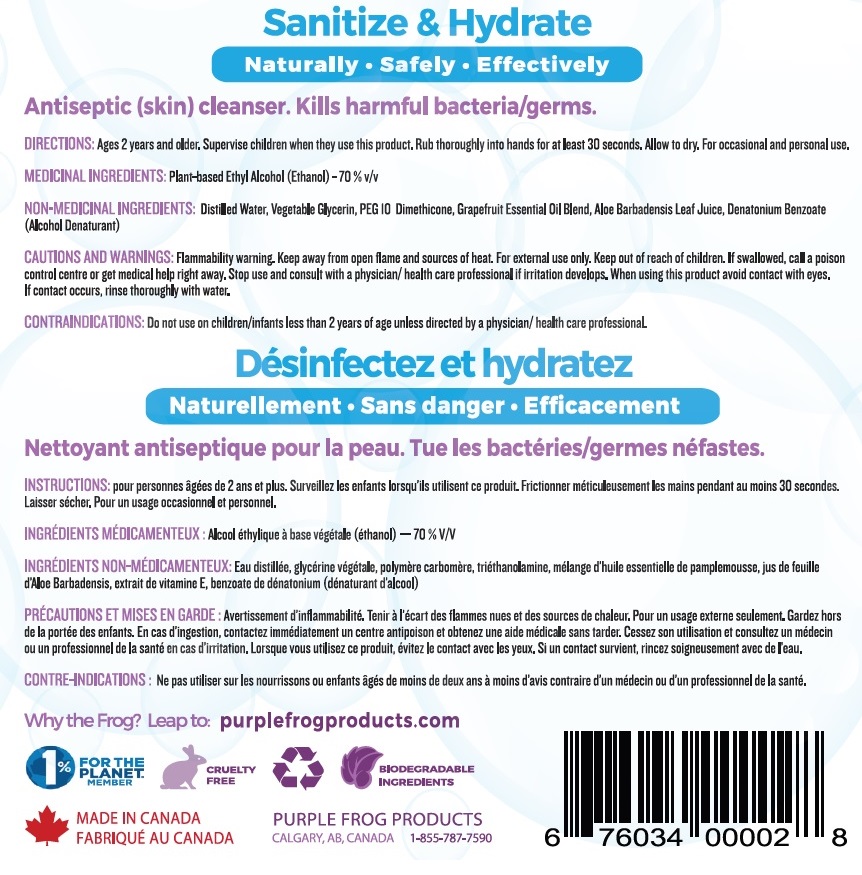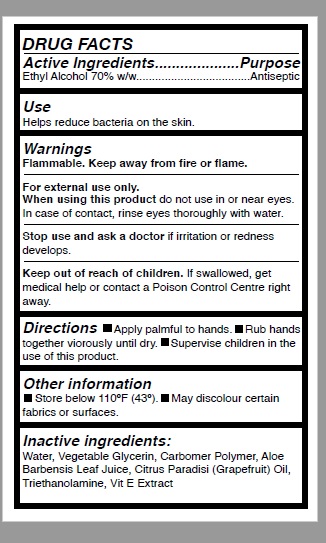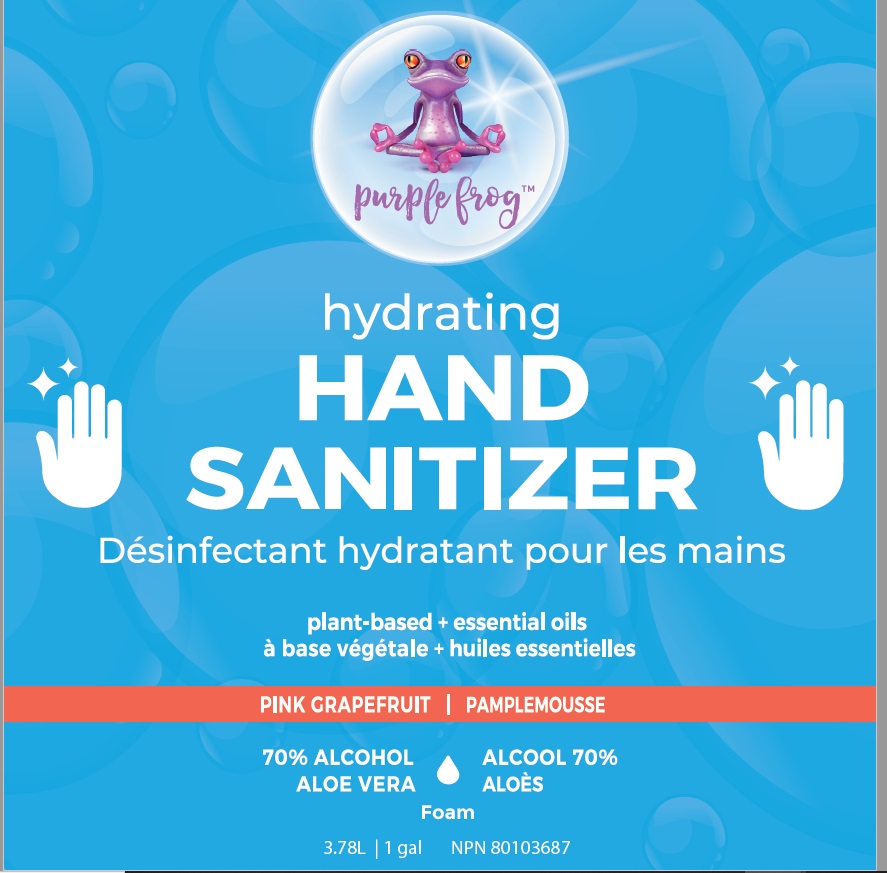 DRUG LABEL: Hydrating Hand Saintizer
NDC: 80382-001 | Form: AEROSOL, FOAM
Manufacturer: Natural Distributions Ltd. o/a Purple Frog Products Suite
Category: otc | Type: HUMAN OTC DRUG LABEL
Date: 20201124

ACTIVE INGREDIENTS: ALCOHOL 70 mL/100 mL
INACTIVE INGREDIENTS: GLYCERIN; DIMETHICONE PEG-10 PHOSPHATE; DENATONIUM BENZOATE; WATER; ALOE VERA LEAF; GRAPEFRUIT OIL

Hydrating Hand Sanitizer: foam

ACTIVE INGREDIENT

Ethyl Alcohol 70%

Purpose -Antiseptic Skin cleanser

Use

- Antiseptic Skin cleanser

Warnings

Keep away from open flame & sources of heat.

For extenal use only.

Keep out of children

If accidently swallowed, call a posion control center or get medical help right away.

USER SAFETY WARNINGS

Do not get into eyes

If contact occurs, rinse thoroughly with water

DOSAGE AND ADMINISTRATION

- Children,adolescents and adults 2 years and over.
- for occasional and personal domestic use
- supervise children when they use this product.
- Place enough product on your plam to thoroughly cover your hands.
- rub thoroughly into hands for at least 30 seconds
- Allow to dry.

Other Information

- May discolor certain fabrics or surfaces
- do not store above 110 F (43 C)

INACTIVE INGREDIENT

Distilled Water, Vegetable Glycerin, PEG 10 Dimethicone, Grapefruit Essential Oil Blend, Aloe Barbadensis Leaf Juice, Denatonium Benzoate.